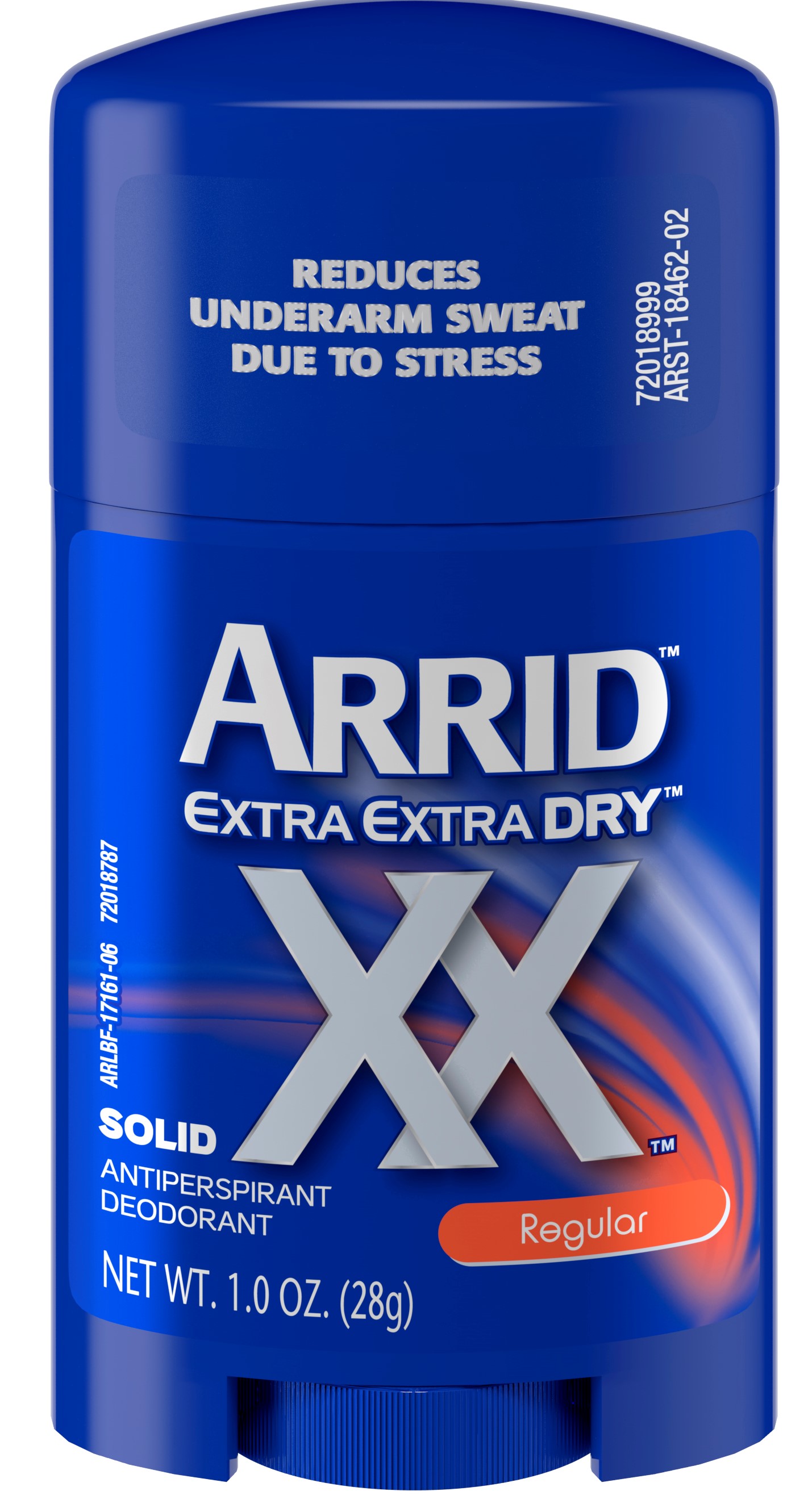 DRUG LABEL: Arrid Extra Extra Dry Regular Solid
NDC: 10237-865 | Form: STICK
Manufacturer: Church & Dwight Co., Inc.
Category: otc | Type: HUMAN OTC DRUG LABEL
Date: 20241120

ACTIVE INGREDIENTS: ALUMINUM CHLOROHYDRATE 0.19 g/1 g
INACTIVE INGREDIENTS: HYDROGENATED CASTOR OIL; PPG-14 BUTYL ETHER; CYCLOMETHICONE 5; STEARYL ALCOHOL; FD&C BLUE NO. 1; ALKYL (C12-15) BENZOATE; TALC; PETROLATUM; LAURETH-4

Arrid Extra Extra Dry Regular Solid

ACTIVE INGREDIENT

Aluminum Chlorohydrate 19%

PURPOSE

Antiperspirant

INDICATIONS AND USAGE

Usereduces underarm perspiration

WARNINGS

For external use only

Do not use on broken skin

Stop use if rash or irritation occurs

Ask a doctor before use if you have kidney disease

Keep out of reach of children.

If swallowed, get medical help or contact a Poison Control Center right away.

Directions

Apply a thin layer to underarms only

INACTIVE INGREDIENT

PPG-14 Butyl Ether, Cyclopentasiloxane, Stearyl Alcohol, C12-15 Alkyl Benzoate, Talc, Hydrogenated Castor Oil, Petrolatum, Fragrance, Laureth-4, Blue 1.

QUESTIONS

? 1-800-248-8820

M-F 9-5 ET

Manufactured by

Church & Dwight Co.,

Inc. Ewing, NJ 08628

www.arrid.com

PACKAGE LABEL

REDUCES

UNDERARM SWEAT

DUE TO STRESS

ARRID

EXTRA EXTRA DRY

XX

Regular

SOLID

ANTIPERSPIRANT

DEODORANT

NEW WT. 1.0 OZ. (28g)